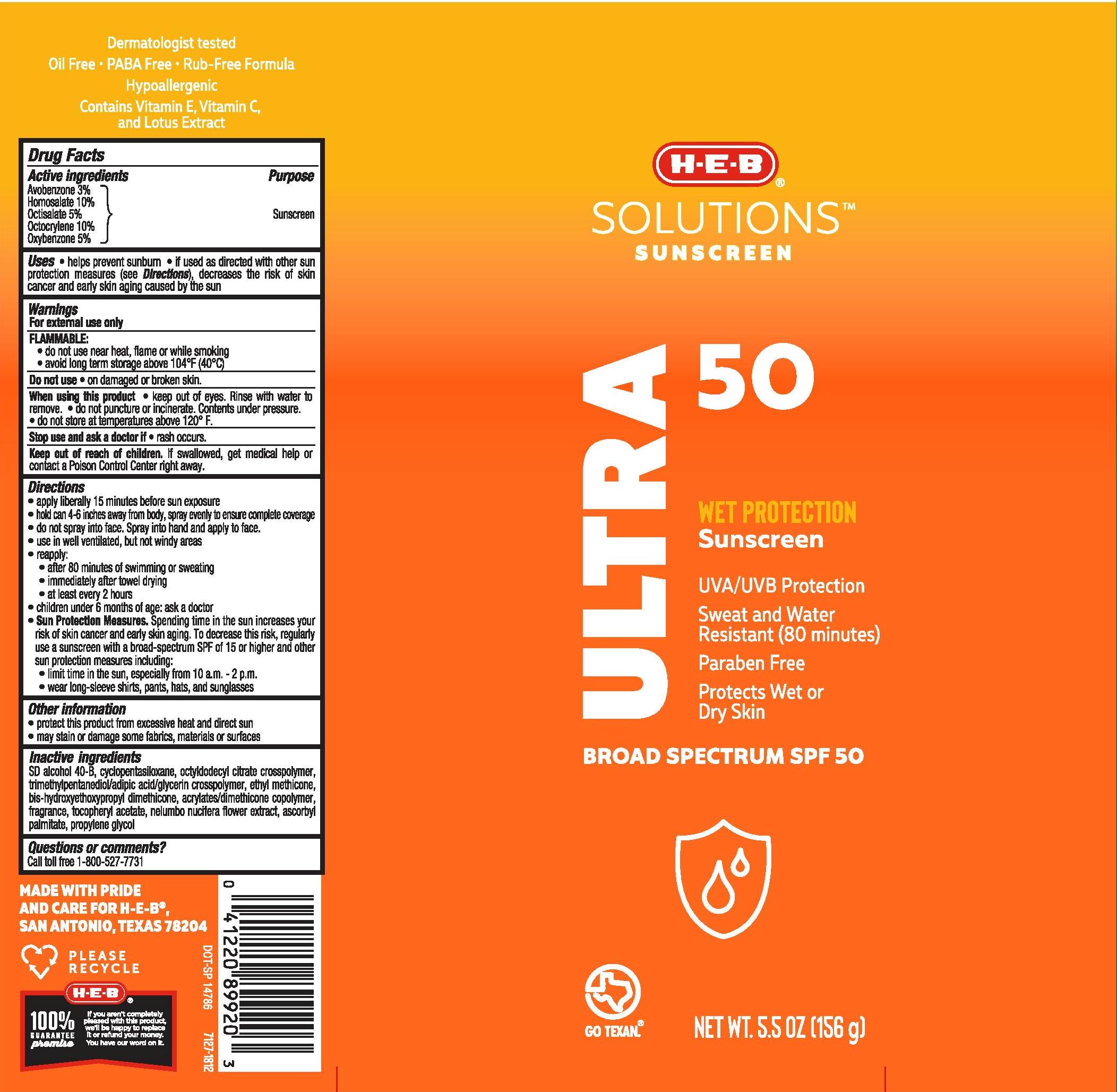 DRUG LABEL: H.E.B
NDC: 37808-965 | Form: AEROSOL, SPRAY
Manufacturer: H.E.B
Category: otc | Type: HUMAN OTC DRUG LABEL
Date: 20241015

ACTIVE INGREDIENTS: AVOBENZONE 30 mg/1 g; HOMOSALATE 100 mg/1 g; OCTISALATE 50 mg/1 g; OCTOCRYLENE 100 mg/1 g; OXYBENZONE 50 mg/1 g
INACTIVE INGREDIENTS: ALCOHOL; CYCLOMETHICONE 5; OCTYLDODECYL CITRATE CROSSPOLYMER; TRIMETHYLPENTANEDIOL/ADIPIC ACID/GLYCERIN CROSSPOLYMER (25000 MPA.S); ETHYL METHICONE (8 MPA.S); BIS-HYDROXYETHOXYPROPYL DIMETHICONE (50 CST); .ALPHA.-TOCOPHEROL ACETATE; NELUMBO NUCIFERA FLOWER; ASCORBYL PALMITATE; PROPYLENE GLYCOL

H.E.B Solutions Sunscreen Ultra SPF 50 Continuous Spray

Active ingredients

Avobenzone 3.0%, Homosalate 10.0%, Octisalate 5.0%, Octocrylene 10.0%, Oxybenzone 5.0%

Purpose

Sunscreen

Uses

- helps prevent sunburn
- if used as directed with other sun protection measures (see Directions), decreases the risk of skin cancer and early skin aging caused by the sun

Warnings

For external use only

FLAMMABLE:

• do not use near heat, flame or while smoking

• avoid long term storage above 104°F (40°C)

Do not use • on damaged or broken skin.

When using this product • keep out of eyes. Rinse with water to remove. • do not puncture or incinerate. Contents under pressure. • do not store at temperatures above 120°F.

Stop use and ask a doctor if • rash occurs.

Keep out of reach of children. If swallowed, get medical help or contact a Poison Control Center right away.

Directions

- apply liberally 15 minutes before sun exposure
- hold can 4-6 inches away from body, spray evenly to ensure complete coverage
- do not spray into face. Spray into hand and apply to face.
- use in well ventilated, but not windy areas
- reapply:

• after 80 minutes of swimming or sweating
• immediately after towel drying
• at least every 2 hours

- children under 6 months of age: ask a doctor
- Sun Protection Measures. Spending time in the sun increases your risk of skin cancer and early skin aging. To decrease this risk, regularly use a sunscreen with a broad-spectrum SPF of 15 or higher and other sun protection measures including:

• limit time in the sun, especially from 10 a.m. - 2 p.m.

• wear long-sleeve shirts, pants, hats, and sunglasses

Other information

- protect this product from excessive heat and direct sun
- may stain or damage some fabrics, materials or surfaces

Inactive ingredients

SD alcohol 40-B, cyclopentasiloxane, octyldodecyl citrate crosspolymer, trimethylpentanediol/adipic acid/ glycerin crosspolymer, ethyl methicone, bis-hydroxyethoxypropyl dimethicone, acrylates/dimethicone copolymer, fragrance, tocopheryl acetate, nelumbo nucifera flower extract, ascorbyl palmitate, propylene glycol

Questions or comments?

Call toll free 1-800-527-7731

PACKAGE LABEL

H.E.B Solutions Sunscreen Ultra SPF 50 Continuous Spray

5.5 OZ (156g)

NDC 37808-965-37